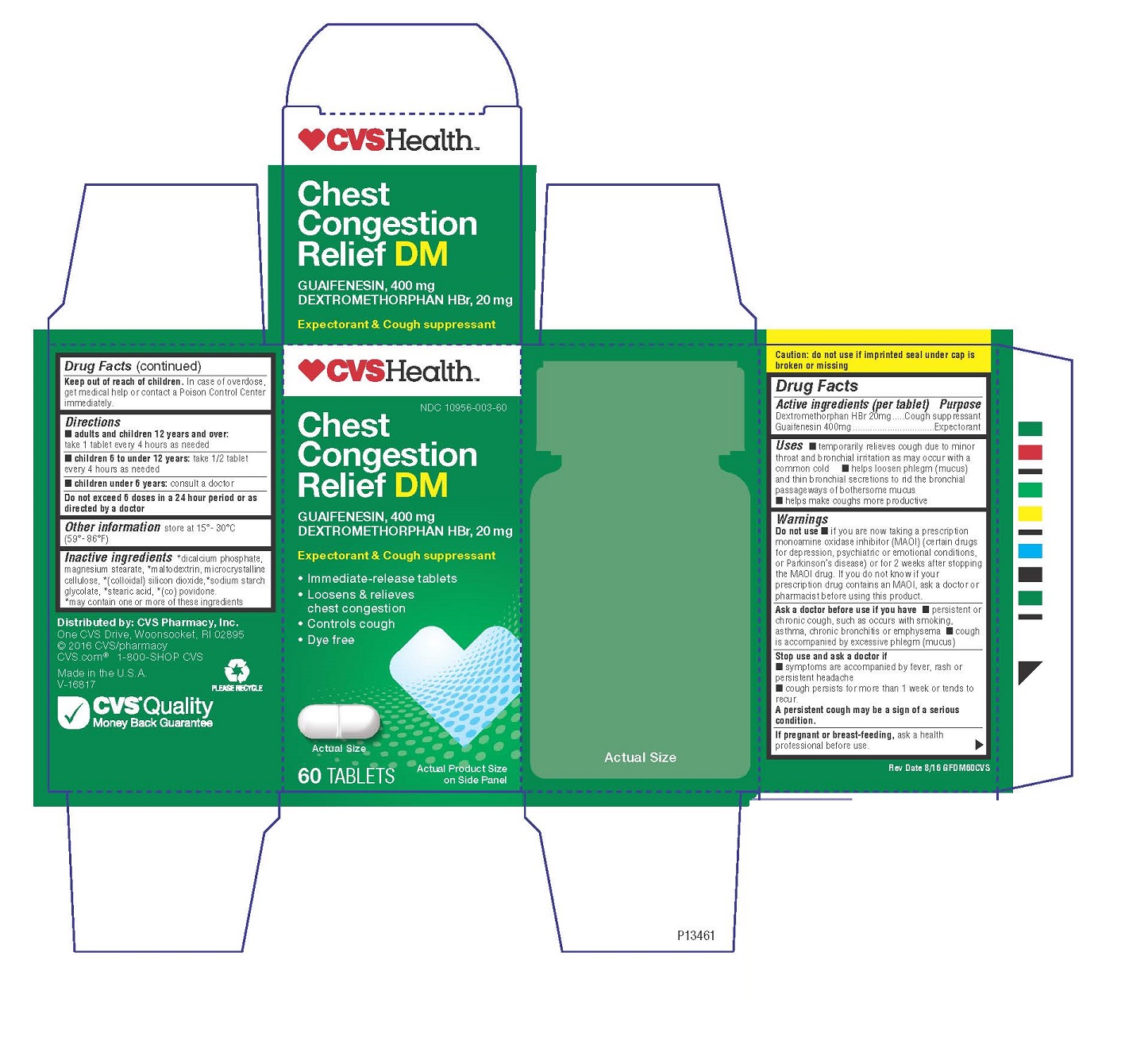 DRUG LABEL: CVS Chest Congestion Relief
NDC: 69842-996 | Form: TABLET
Manufacturer: CVS Pharmacy, Inc.
Category: otc | Type: HUMAN OTC DRUG LABEL
Date: 20241218

ACTIVE INGREDIENTS: DEXTROMETHORPHAN HYDROBROMIDE 20 mg/1 1; Guaifenesin 400 mg/1 1
INACTIVE INGREDIENTS: MAGNESIUM STEARATE; CELLULOSE, MICROCRYSTALLINE; SILICON DIOXIDE; COPOVIDONE; MALTODEXTRIN; STEARIC ACID

Drug Facts CVS Congestion Relief DM

Active ingredient - (per tablet)

Dextromethorphan Hydrobromide 20mg Cough Suppressant
Guaifenesin 400mg Expectorant

Ask doctor before use if you have

persistent or chronic cough, such as occurs with smoking, asthma, bronchitis or emphysma

cough is accompanied by excessive phlegm (mucous)

Stop use and ask doctor if

Symptoms are accompanied by fever, rash or persistent headache

cough persists for more than 1 week or tends to recur

A persistent cough may be a sign of a serious condition

Do not use if you are now taking a prescription monoamine oxidase (inhiMor~MAIO)

Certain drugs for depression, psychiatric or emotional conditioners or Parkinson's disease

or for 2 weeks after stopping MAIO drug, If you do not know if your prescription drug contains

an MAIO, ask your doctor or pharmacist before using this product.

Keep out of reach of children, In ase of overdose, get medical help or contact a Poison Center immediately

PREGNANCY OR BREAST FEEDING

If pregnant or breastfeeding, ask a health professional before use.

INACTIVE INGREDIENT

magnesium stearate, microcrystalline cellulose,
colloidal silicon dioxide, (co) povidone, dicalcium
phosphate, maltodextrin, sodium starch glycolate, stearic acid

Directions
• Adults and children 12 years of age and over:
take 1 tablet every 4 hours as needed
• Children 610 under 12 years of age: take 1/2 tablet every 4 hours as needed
• Children under 6 years of age: consult a doctor
Do not exceed 6 doses in a 24 hour period or as directed by a doctor
Other information store at 15'- 30' C (59'- 86'F) Rev 10/U9 RCCF

INDICATIONS AND USAGE

Uses. temporarily relieves cough due to minor throat and bronchial irritation
as may occur with a common cold • helps loosen phlegm (mucus) and thin
bronchial secretions to rid the bronchial passageways of bothersome mucus
• helps make coughs more productive

Purpose

Cough Suppressant

Expectorant

Do not use if you are now taking a prescription monoamine oxidase (inhiMor~MAIO)

Certain drugs for depression, psychiatric or emotional conditioners or Parkinson's disease

or for 2 weeks after stopping MAIO drug, If you do not know if your prescription drug contains

an MAIO, ask your doctor or pharmacist before using this product.

PACKAGE LABEL

Enter section text here